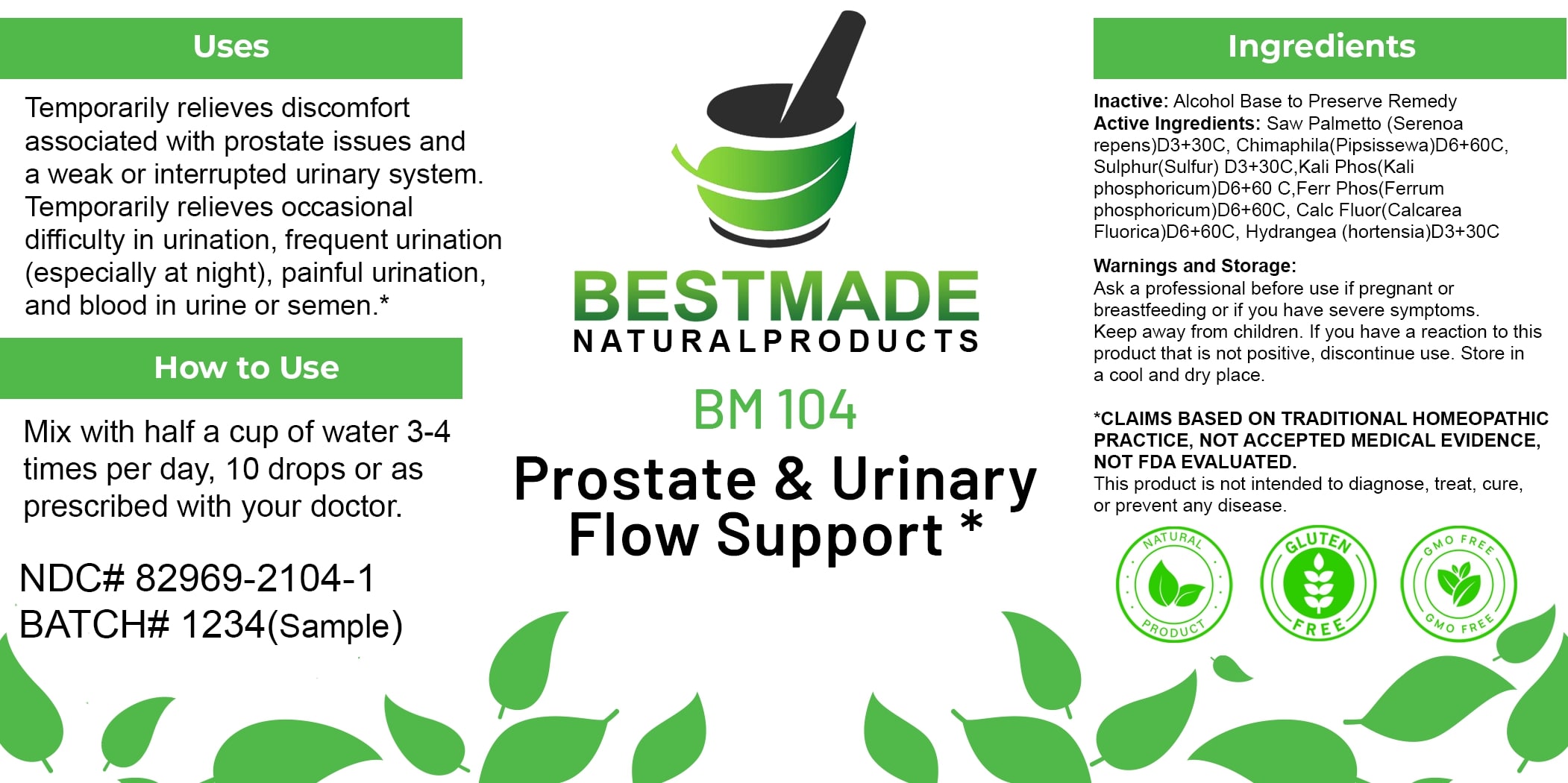 DRUG LABEL: Bestmade Natural Products BM104
NDC: 82969-2104 | Form: LIQUID
Manufacturer: Bestmade Natural Products
Category: homeopathic | Type: HUMAN OTC DRUG LABEL
Date: 20250207

ACTIVE INGREDIENTS: SULFUR 30 [hp_C]/30 [hp_C]; DIBASIC POTASSIUM PHOSPHATE 30 [hp_C]/30 [hp_C]; FERROSOFERRIC PHOSPHATE 30 [hp_C]/30 [hp_C]; SAW PALMETTO 30 [hp_C]/30 [hp_C]; HYDRANGEA ARBORESCENS ROOT 30 [hp_C]/30 [hp_C]; CALCIUM FLUORIDE 30 [hp_C]/30 [hp_C]; CHIMAPHILA UMBELLATA 30 [hp_C]/30 [hp_C]
INACTIVE INGREDIENTS: ALCOHOL 30 [hp_C]/30 [hp_C]

BM104

DOSAGE AND ADMINISTRATION

How to Use

Mix with half a cup of water 3-4 times per day, 10 drops or as prescribed with your doctor.

INACTIVE INGREDIENT

Ingredients

Inactive: Alcohol Base to Preserve Remedy

ACTIVE INGREDIENT

Active Ingredients: Saw Palmetto (Serenoa repens) D3+30C, Chimaphila (Pipsissewa) D6+60C, Sulphur (Sulfur) D3+30C, Kali Phos (Kali phosphoricum) D6+60 C Ferr Phos (Ferrum phosphoricum) D6+60C, Calc Fluor (Calcarea Fluorica) D6+60C, Hydrangea (hortensia) D3+30C

Uses

Temporarily relieves discomfort associated with prostate issues and a weak or interrupted urinary system. Temporarily relieves occasional difficulty in urination, frequent urination (especially at night), painful urination, and blood in urine or semen.*

*CLAIMS BASED ON TRADITIONAL HOMEOPATHIC PRACTICE, NOT ACCEPTED MEDICAL EVIDENCE, NOT FDA EVALUATED.

This product is not intended to diagnose, treat, cure, or prevent any disease.

Uses

Temporarily relieves discomfort associated with prostate issues and a weak or interrupted urinary system. Temporarily relieves occasional difficulty in urination, frequent urination (especially at night), painful urination, and blood in urine or semen.*

*CLAIMS BASED ON TRADITIONAL HOMEOPATHIC PRACTICE, NOT ACCEPTED MEDICAL EVIDENCE, NOT FDA EVALUATED.

This product is not intended to diagnose, treat, cure, or prevent any disease.

KEEP OUT OF REACH OF CHILDREN

Warnings and Storage:

Ask a professional before use if pregnant or breastfeeding or if you have severe symptoms. Keep away from children. If you have a reaction to this product that is not positive, discontinue use. Store in a cool and dry place.

Warnings and Storage:

Ask a professional before use if pregnant or breastfeeding or if you have severe symptoms. Keep away from children. If you have a reaction to this product that is not positive, discontinue use. Store in a cool and dry place.

*CLAIMS BASED ON TRADITIONAL HOMEOPATHIC PRACTICE, NOT ACCEPTED MEDICAL EVIDENCE, NOT FDA EVALUATED.

This product is not intended to diagnose, treat, cure, or prevent any disease.

Entire package label